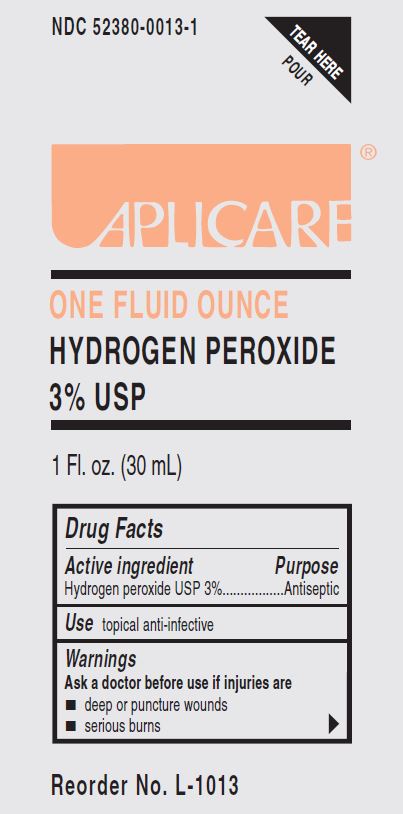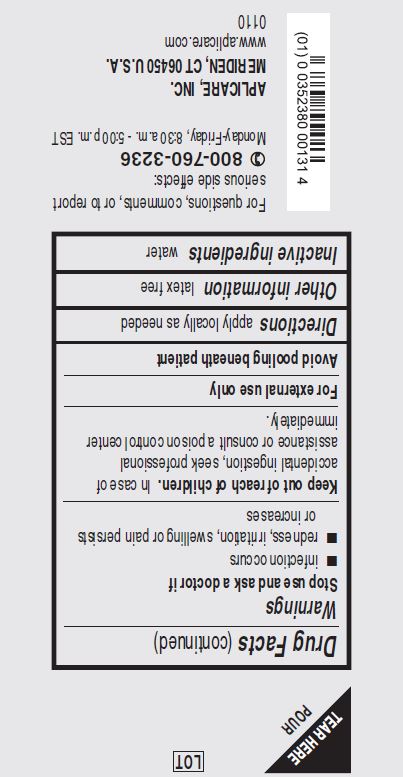 DRUG LABEL: Aplicare Hydrogen Peroxide
NDC: 52380-0013 | Form: LIQUID
Manufacturer: Aplicare Products, LLC
Category: otc | Type: HUMAN OTC DRUG LABEL
Date: 20231018

ACTIVE INGREDIENTS: HYDROGEN PEROXIDE 3 mL/100 mL
INACTIVE INGREDIENTS: WATER

0013 Aplicare Hydrogen Peroxide

Active ingredient

Hydrogen peroxide USP 3%

Purpose

First Aid Antiseptic

Use

- topical anti-infective

Warnings

For external use only.

Avoid pooling beneath patient

Ask a doctor before use if injuries are

- • deep or puncture wounds
- • serious burns

Stop use and ask a doctor if

- • infection occurs
- • redness, irritation, swelling or pain persists or increases

Keep out of reach of children.

In case of accidental ingestion, seek professional assistance or consult a poison control center immediately.

Directions

- • apply locally as needed

Other information

- • not made with natural rubber latex
- • protect from freezing, avoid excessive heat

Inactive ingredients

- water

Manufacturing Information

Manufactured by:

Aplicare Products, LLC.

550 Research Parkway, Meriden, CT 06450 USA

1-800-633-5463
0110

Recent Major Changes

- Indications and Usage
- Warnings and Precautions
- Dosage and Administration